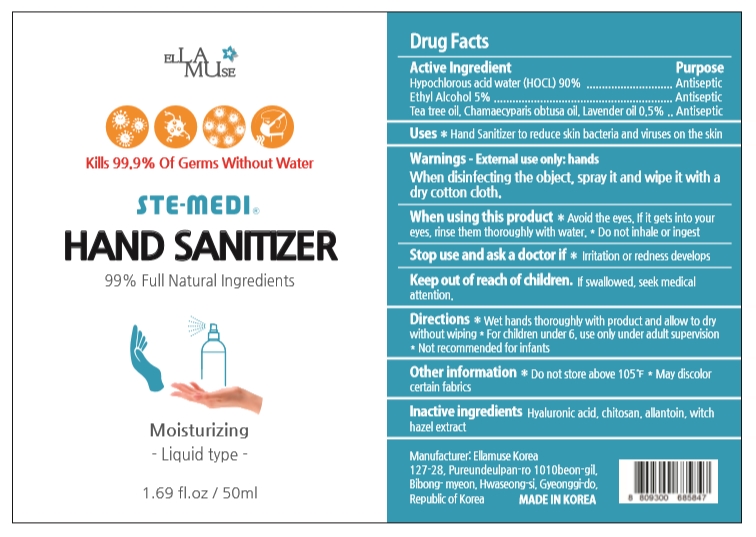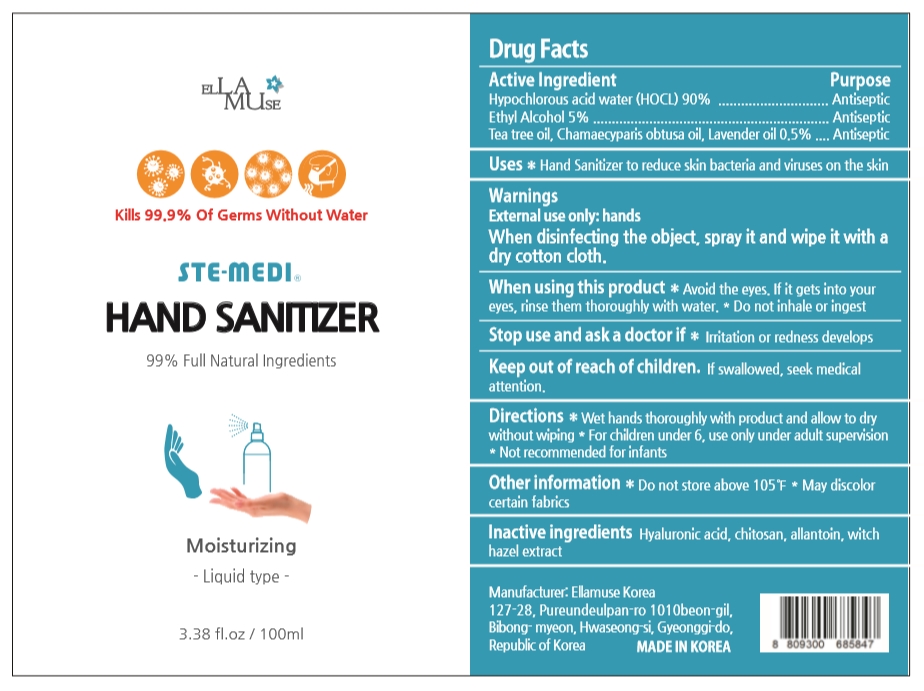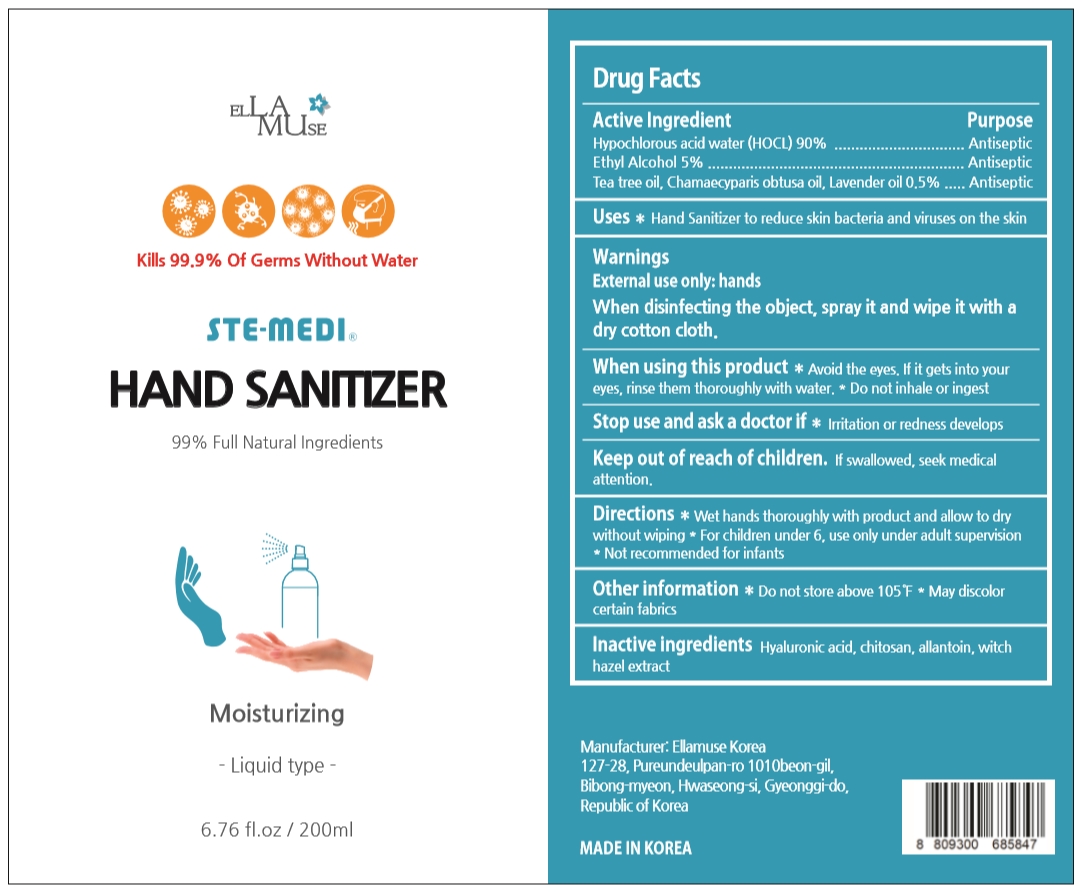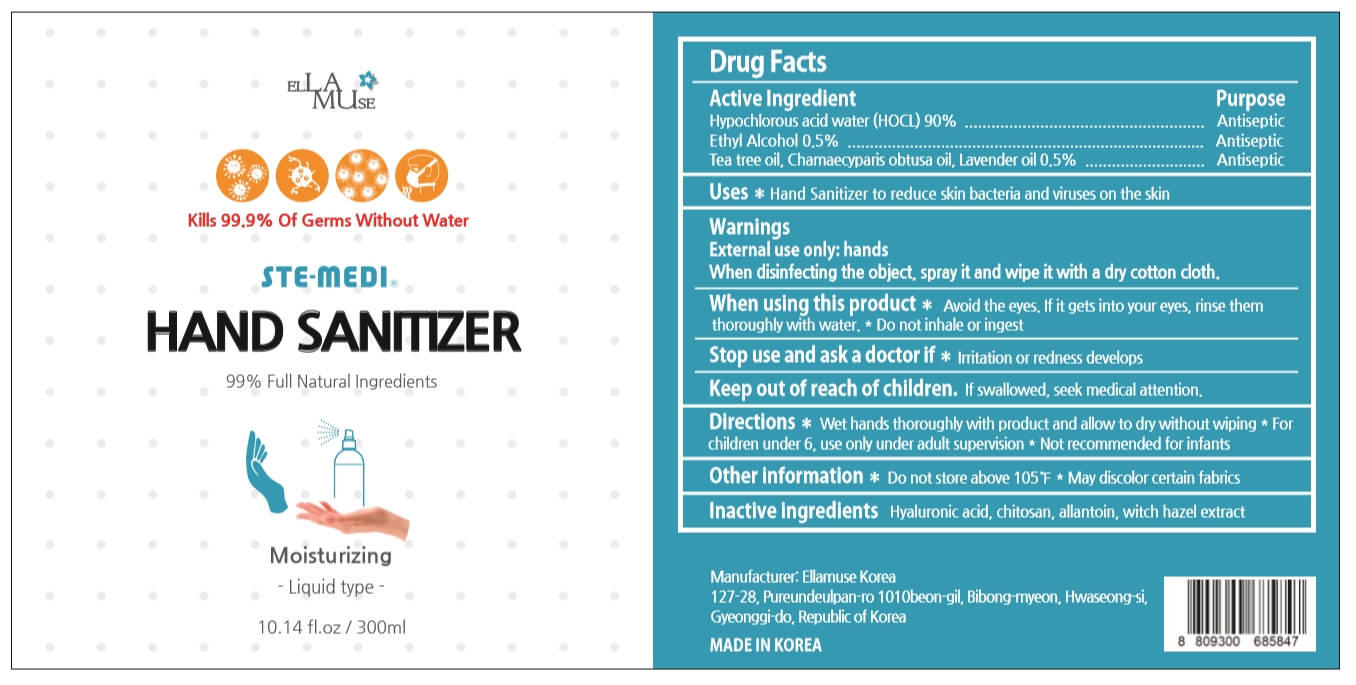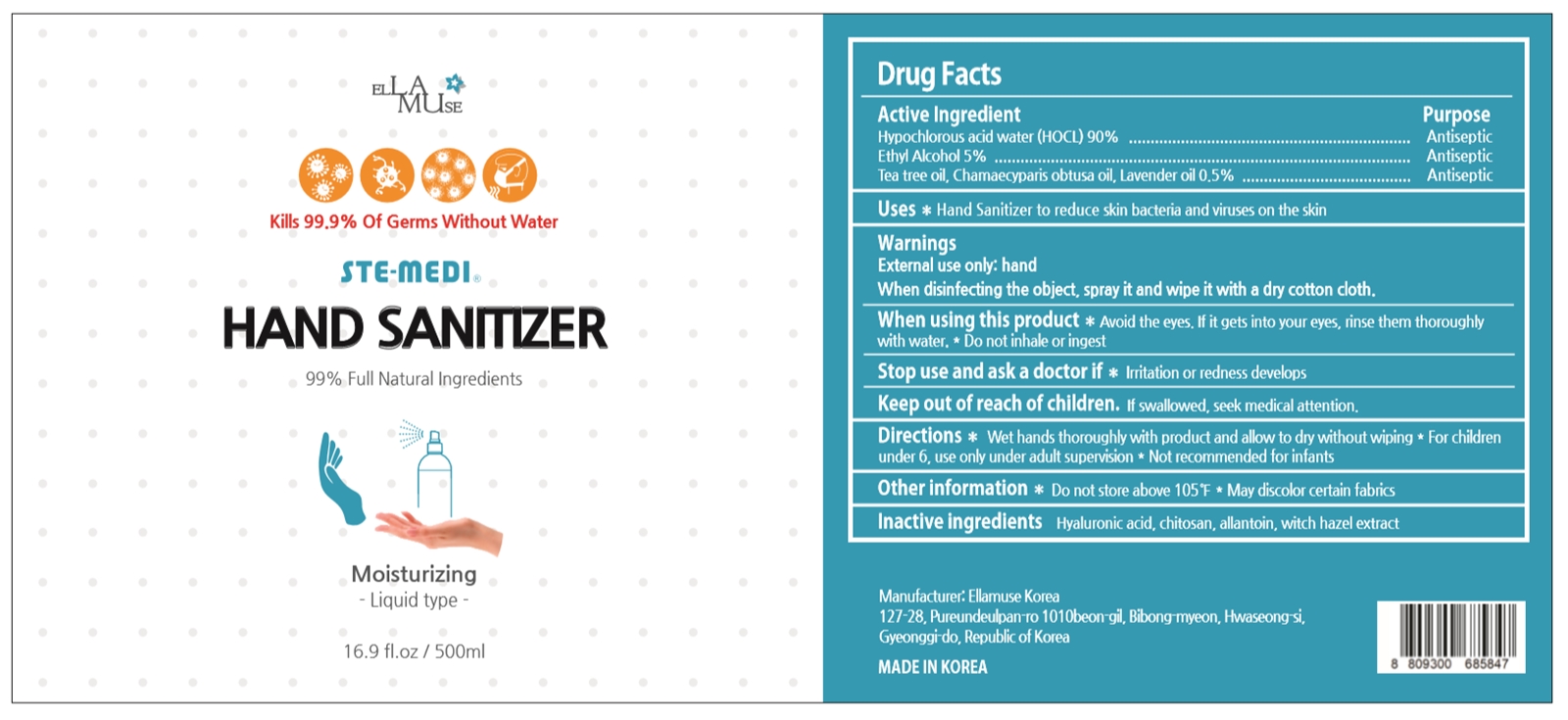 DRUG LABEL: STE-MEDI
NDC: 77599-202 | Form: LIQUID
Manufacturer: ELLAMUSE KOREA
Category: otc | Type: HUMAN OTC DRUG LABEL
Date: 20200604

ACTIVE INGREDIENTS: HYPOCHLOROUS ACID 90 g/100 mL; TEA TREE OIL 0.2 g/100 mL; CHAMAECYPARIS OBTUSA WOOD OIL 0.15 g/100 mL; LAVENDER OIL 0.15 g/100 mL; ALCOHOL 5 mL/100 mL
INACTIVE INGREDIENTS: HYALURONIC ACID; POLIGLUSAM HYDROCHLORIDE; ALLANTOIN; WITCH HAZEL

77599-202

Active Ingredient

Hypochlorous acid water (HOCL) 90%

Ethyl Alcohol 5%

Tea tree oil 0.2%, Chamaecyparis obtusa oil 0.15%, Lavender oil 0.15%

Purpose

Antiseptic

Uses

Hand Sanitizer to reduce skin bacteria and viruses on the skin

Warnings

External use only: hand

When disinfecting the object, spray it and wipe it with a dry cotton cloth.

When using this product

Avoid the eyes. If it gets into your eyes, rinse them thoroughly with water.

Do not inhale or ingest.

Stop use and ask a doctor if

Irritation or redness develops

Keep out of reach of children.

If swallowed, seek medical attention.

Directions

Wet hands thoroughly with product and allow to dry without wiping

For children under 6, use only adult supervision

Not recommended for infants

Other information

Do not store above 105F

May discolor certain fabrics

Inactive ingredients

Hyaluronic acid, chitosan, allantoin, witch hazel extract